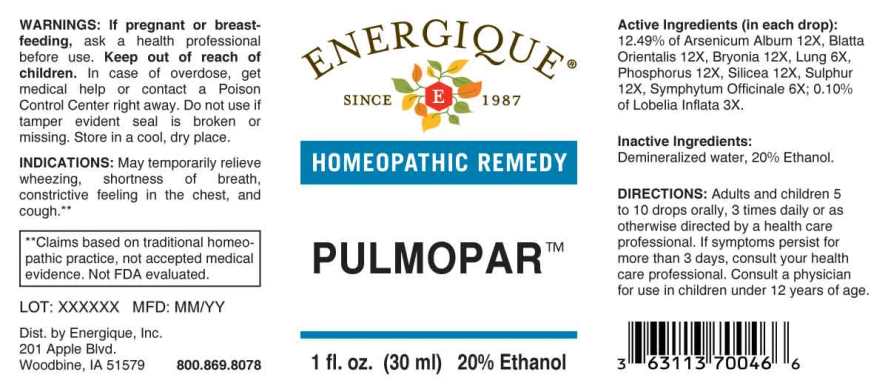 DRUG LABEL: Pulmopar
NDC: 44911-0592 | Form: LIQUID
Manufacturer: Energique, Inc.
Category: homeopathic | Type: HUMAN OTC DRUG LABEL
Date: 20241029

ACTIVE INGREDIENTS: LOBELIA INFLATA WHOLE 3 [hp_X]/1 mL; SUS SCROFA LUNG 6 [hp_X]/1 mL; COMFREY ROOT 6 [hp_X]/1 mL; ARSENIC TRIOXIDE 12 [hp_X]/1 mL; BLATTA ORIENTALIS 12 [hp_X]/1 mL; BRYONIA ALBA WHOLE 12 [hp_X]/1 mL; PHOSPHORUS 12 [hp_X]/1 mL; SILICON DIOXIDE 12 [hp_X]/1 mL; SULFUR 12 [hp_X]/1 mL
INACTIVE INGREDIENTS: WATER; ALCOHOL

DRUG FACTS:

ACTIVE INGREDIENTS:

(in each drop) 12.49% of Arsenicum Album 12X, Blatta Orientalis 12X, Bryonia (Alba) 12X, Lung (Suis) 6X, Phosphorus 12X, Silicea 12, Sulphur 12X, Symphytum Officinale 6X; 0.10% of Lobelia Inflata 3X.

INDICATIONS:

May temporarily relieve wheezing, shortness of breath, constrictive feeling in the chest and cough.**

**Claims based on traditional homeopathic practice, not accepted medical evidence. Not FDA evaluated.

WARNINGS:

If pregnant or breastfeeding, ask a health professional before use.

Keep out of reach of children. In case of overdose, get medical help or contact a Poison Control Center right away.

Do not use if tamper evident seal is broken or missing.

Store in a cool, dry place

Keep out of reach of children. In case of overdose, get medical help or contact a Poison Control Center right away.

DIRECTIONS:

Adults and children 5 to 10 drops orally, 3 times daily or as otherwise directed by a health care professional. If symptoms persist for more than 3 days, consult your health care professional. Consult a physician for use in children under 12 years of age.

INDICATIONS:

May temporarily relieve wheezing, shortness of breath, constrictive feeling in the chest and cough.**

**Claims based on traditional homeopathic practice, not accepted medical evidence. Not FDA evaluated.

INACTIVE INGREDIENTS:

Demineralized water, 20% Ethanol

QUESTIONS:

Dist. by Energique, Inc.
201 Apple Blvd.
Woodbine, IA 51579 800.869.8078

PACKAGE LABEL DISPLAY:

ENERGIQUE
SINCE 1987
HOMEOPATHIC REMEDY
PULMOPAR
1 fl. oz. (30 ml)